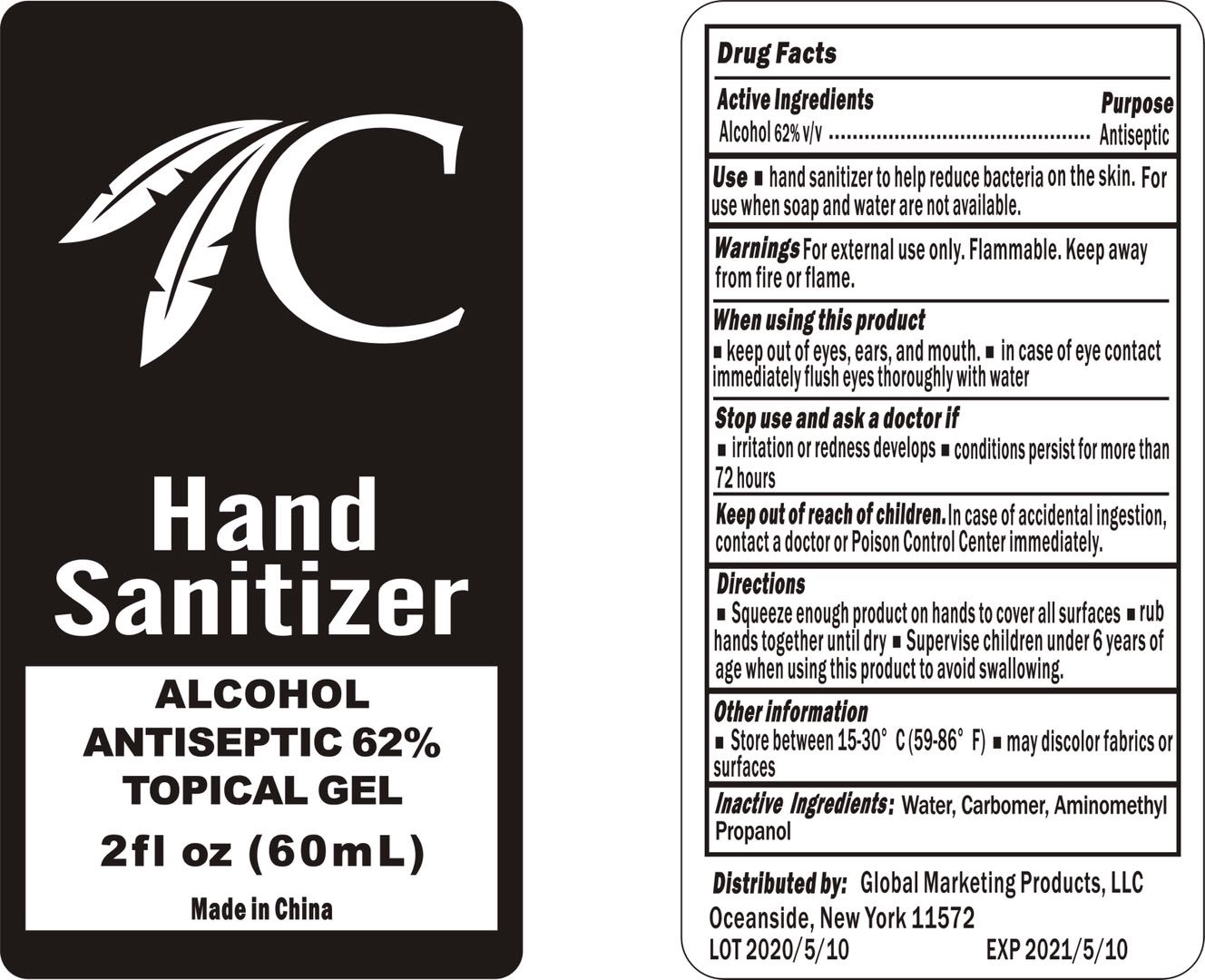 DRUG LABEL: Choctaw Hand Sanitizer
NDC: 75255-006 | Form: GEL
Manufacturer: Guangzhou Baoli Cosmetics Co., Ltd.
Category: otc | Type: HUMAN OTC DRUG LABEL
Date: 20200518

ACTIVE INGREDIENTS: ALCOHOL 62 mL/100 mL
INACTIVE INGREDIENTS: water; TROLAMINE; GLYCERIN; AMINOMETHYLPROPANOL

Active ingredient

Alcohol 62% v/v

Purpose

Antiseptic

Use

- hand sanitizer to help reduce bacteria on the skin. For use when soap and water are not available.

KEEP OUT OF REACH OF CHILDREN

In case of accidental ingestion, contact a doctor or Poison Control Center immediately.

Warning

For external use only

Flammable, keep away from fire or flame.

When using this product

- keep out of eyes, ears, and mouth.
- In case of eye contact immediately flush eyes thoroughly with water.

Stop use and ask a doctor if

- irritation or redness develops
- conditions persist for more than 75 hours.

Other Information:

- Store between 15-30 ℃ (59-86℉)
- may discolor fabrics or surfaces

DOSAGE AND ADMINISTRATION

- Squeeze enough product on hands to cover all surfaces
- rub hands together until dry
- supervise children under 6 years of age when using this product to avoid swallowing.

Inactive ingredients

Water, Carbomer, Aminomethyl Propanol